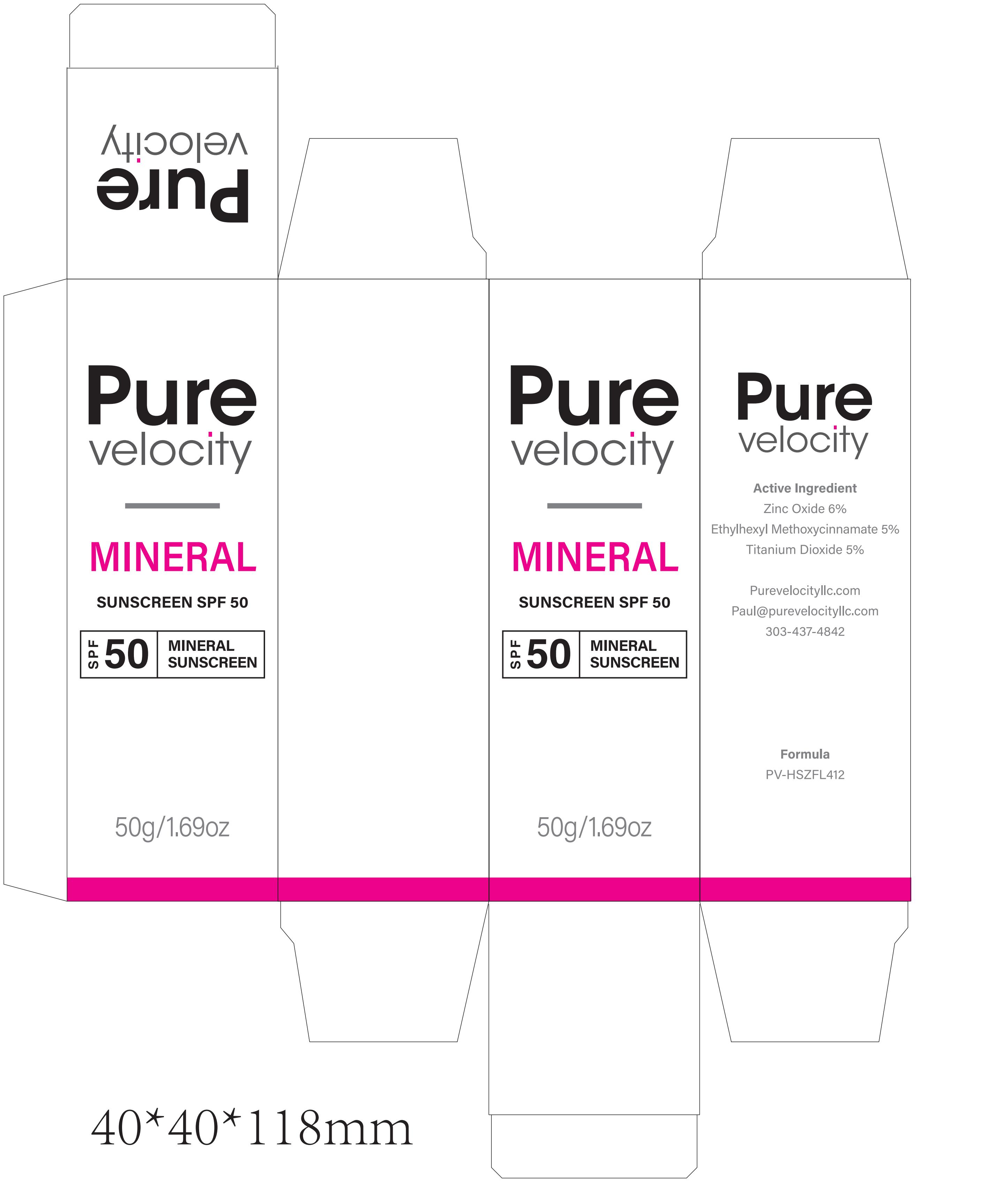 DRUG LABEL: Pure velocity MINERAL SUNSCREEN SPF 50
NDC: 60771-0033 | Form: CREAM
Manufacturer: Guangzhou Haishi Biological Technology Co., Ltd.
Category: otc | Type: HUMAN OTC DRUG LABEL
Date: 20250930

ACTIVE INGREDIENTS: ZINC OXIDE 5.5 g/100 g
INACTIVE INGREDIENTS: BISABOLOL; ETHYLHEXYLGLYCERIN; STEPHANIA TETRANDRA WHOLE; TARAXACUM OFFICINALE (DANDELION) ROOT; SOLANUM LYCOPERSICUM (TOMATO) FRUIT; PARFUMIDINE; MYCOPLASMA FERMENTANS; LILIUM CANDIDUM FLOWER OIL; SAURURUS CHINENSIS WHOLE; WATER; XANTHAN GUM; PROPYLENE GLYCOL DIHEXANOATE; ASCORBIC ACID; ALUMINUM HEXAFLUOROSILICATE; PEG-30 DIPOLYHYDROXYSTEARATE; TOCOPHEROL; DIISOBUTYLPHENOXYETHANOL; DIACYLGLYCEROL OIL; BENTONITE; SODIUM CHLORIDE; DENDROBIUM NOBILE WHOLE; TREMELLA FUCIFORMIS WHOLE; MAGNESIUM STEARATE; CERAMIDE NP; SODIUM HYALURONATE; DIMETHICONE/VINYL DIMETHICONE CROSSPOLYMER (SOFT PARTICLE); DICAPRYLYL CARBONATE; SIMMONDSIA CHINENSIS (JOJOBA) SEED OIL; POLYGLYCERYL-2 TRIISOSTEARATE; ABIES ALBA LEAF OIL; TRIMETHYLSILOXYSILICATE (M/Q 0.66); PHENYL TRIMETHICONE

Active Ingredients

ZINC OXIDE

Purpose

SUNSCREEN

Uses

If used as directed with other sun protection measures(see Directions)，
decreases the risk of skin cancer and early skin aging caused by the sun.

Warnings

For external use only

Stop Use

Rinse with wate to remove.
Stop use and ask doctor if rash occurs.

Do not use on damaged or broken skin.

When Using

When using this product keep out of eyes.

Keep Out Of Reach Of Children

Dosage & administration

Squeeze out an appropriate amount of Sunscreen and spread evenly on skin.

Inactive ingredients

WATER
GLYCEROL
PROPYLENE GLYCOL
SIMMONDSIA CHINENSIS (JOJOBA) SEED OIL
POLYGLYCERYL-2 TRIISOSTEARATE
PHENYL TRIMETHICONE
DICAPRYLYL CARBONATE
TRIMETHYLSILOXYSILICATE
CERA ALBA
DIMETHICONE/VINYL DIMETHICONE CROSSPOLYMER
BENTONITE
SODIUM CHLORIDE
ASCORBIC ACID POLYPEPTIDE
CERAMIDE NP
SPHINGOMONAS FERMENT EXTRACT
SILICA
MAGNESIUM STEARATE
PEG-30 DIPOLYHYDROXYSTEARATE
XANTHAN GUM
SODIUM HYALURONATE
BISABOLOL
TOCOPHEROL
PHENOXYETHANOL
ETHYLHEXYLGLYCERIN
SOLANUM LYCOPERSICUM (Tomato) FRUIT EXTRACT
TREMELLA FUCIFORMIS (Mushroom) EXTRACT
LILIUM CANDIDUM FLOWER EXTRACT
DENDROBIUM NOBILE EXTRACT
STEPHANIA TETRANDRA EXTRACT
TARAXACUM OFFICINALE (Dandelion) LEAF EXTRACT
SAURURUS CHINENSIS LEAF/ROOT EXTRACT
PARFUM